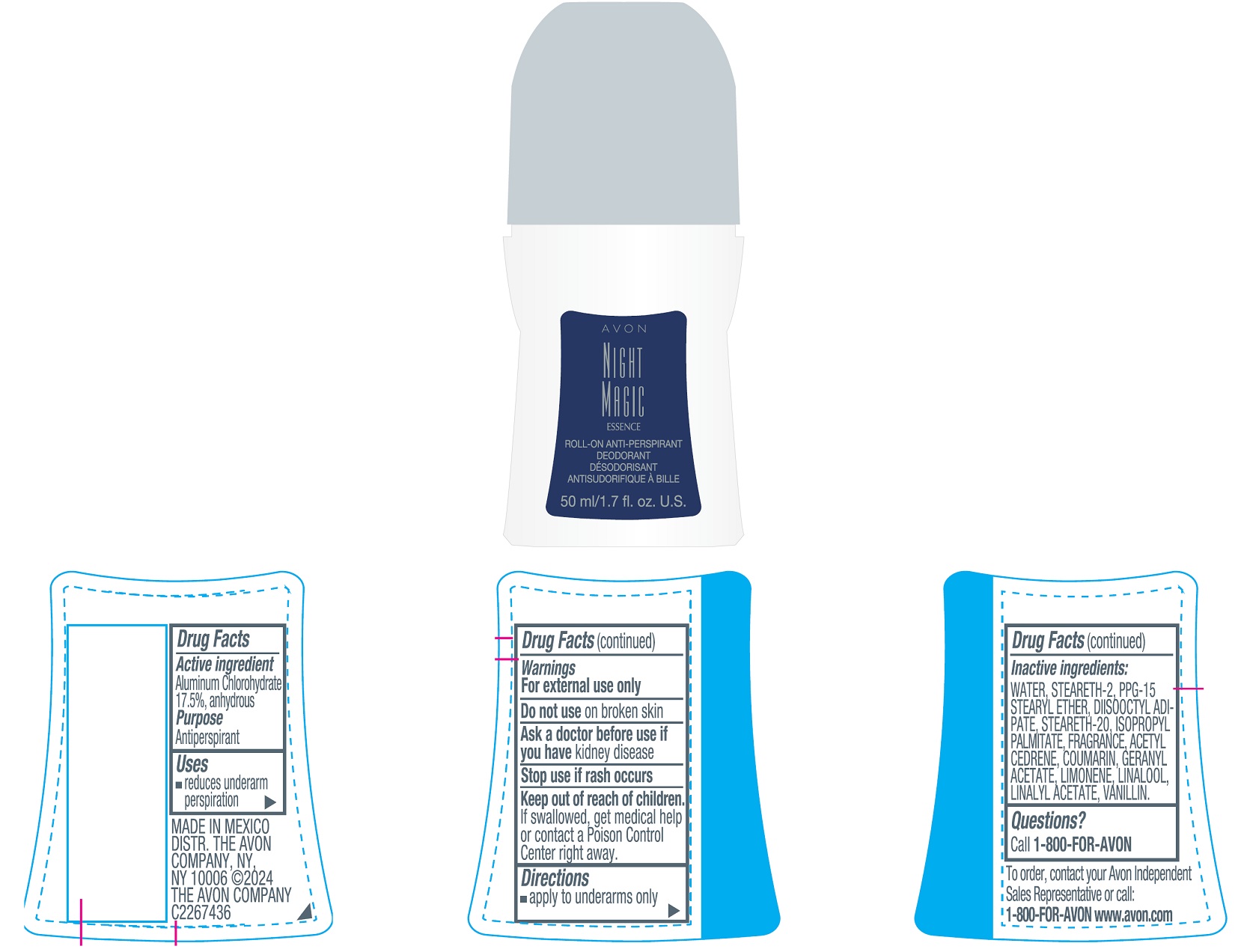 DRUG LABEL: AVON Night Magic Essence
NDC: 71110-1515 | Form: STICK
Manufacturer: Avon Cosmetics Manufacturing, S. de R.L. de C.V.
Category: otc | Type: HUMAN OTC DRUG LABEL
Date: 20241112

ACTIVE INGREDIENTS: ALUMINUM CHLOROHYDRATE 175 mg/1 mL
INACTIVE INGREDIENTS: STEARETH-2; WATER; DIISOOCTYL ADIPATE; PPG-15 STEARYL ETHER; STEARETH-20; ISOPROPYL PALMITATE

AVON Night Magic Essence Roll-On Anti-Perspirant Deodorant 50ml

Active ingredient

Aluminum Chlorohydrate 17.5% anhydrous

Purpose

Antiperspirant

Uses

- reduces underarm perspiration

Warnings

For external use only

Do not useon broken skin

Ask a doctor before use if you havekidney disease

Stop use if rash occurs

Keep out of reach of children.
If swallowed, get medical help or contact a Poison Control Center right away.

Directions

- apply to underarms only

Inactive ingredients

WATER, STEARETH-2, PPG-15 STEARYL ETHER, DIISOOCTYL ADIPATE, STEARETH-20, ISOPROPYL PALMITATE, FRAGRANCE

Questions?

Call 1-800-FOR-AVON

To order, contact your Avon Independent Sales Representative or call:
1-800-FOR-AVON www.avon.com

MADE IN MEXICO
DIST. THE AVON COMPANY, NY, NY 10006
©2024 THE AVON COMPANY C2267436

Principal Display Panel

AVON
NIGHT
MAGIC
ESSENCE
ROLL-ON ANTI-PERSPIRANT
DEODORANT
50 ml/1.7 fl.oz. U.S.